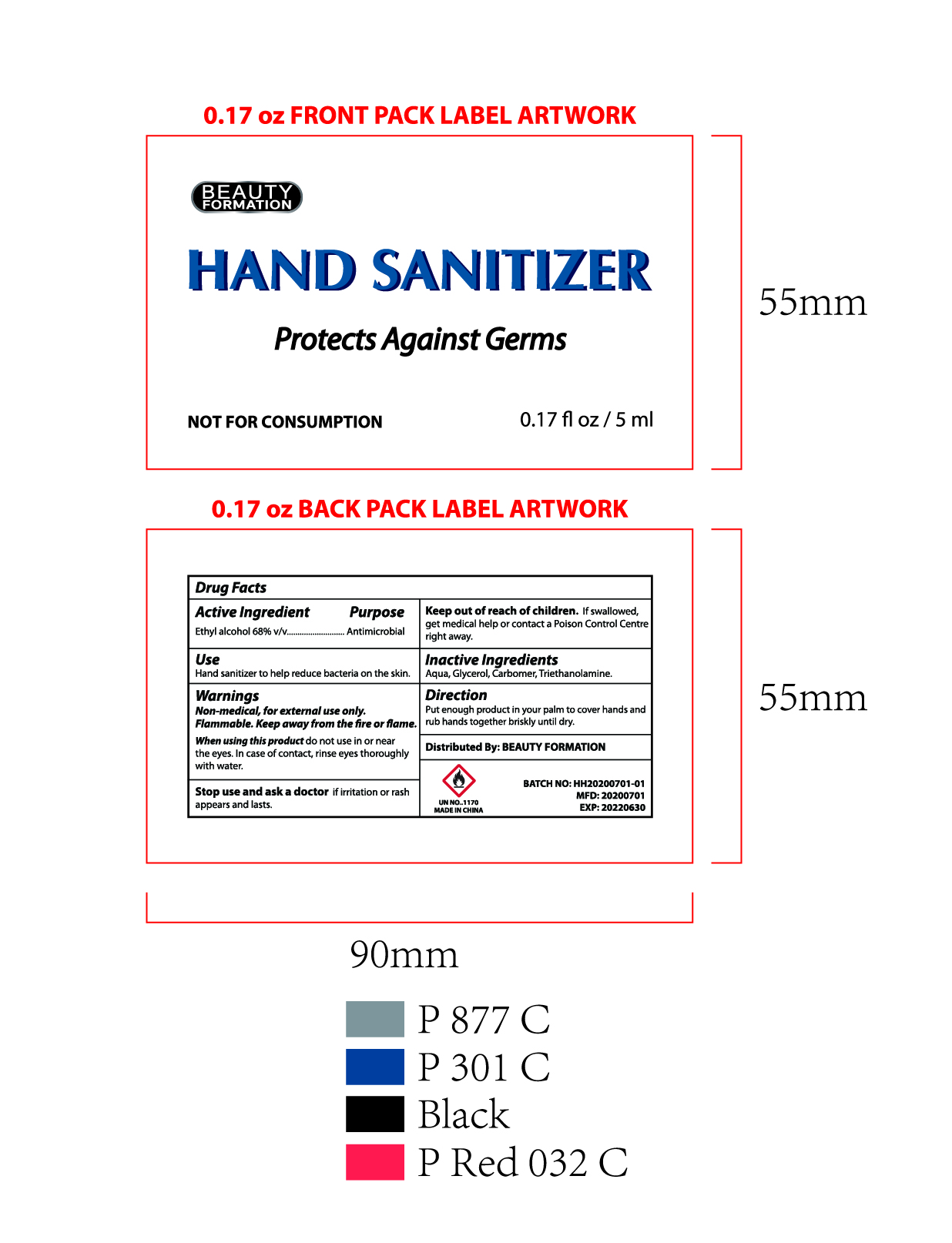 DRUG LABEL: Beauty Formation Hand Sanitizer
NDC: 71004-104 | Form: SOLUTION
Manufacturer: iHotel Guest Amenities Co.,Ltd
Category: otc | Type: HUMAN OTC DRUG LABEL
Date: 20200901

ACTIVE INGREDIENTS: ALCOHOL 68 mL/100 mL
INACTIVE INGREDIENTS: CARBOMER 940; TROLAMINE; GLYCEROL FORMAL

Beauth Formation Hand Sanitizer

ACTIVE INGREDIENT

Ethyl Alcohol 68%

Purpose

Antimicrobial

Use

Hand sanitizer to help reduce bacteria on the skin

Warnings

For external use only.

Non Medical. Flammable. Keep away from fire or flame

When using this product, do not use in or near eyes, In case of contact, rinse eyes thoroughly with water

Stop use and ask a doctor if irritation or rash appears and lasts

Keep out of reach of children. If swallowed, get medical help or contact a poison control center right away

Directions

- Put enough product in your palm to cover hands and rub hands together brisky until dry

Inactive ingredients

Water, Glycerol, Carbomer, Triethanolamine